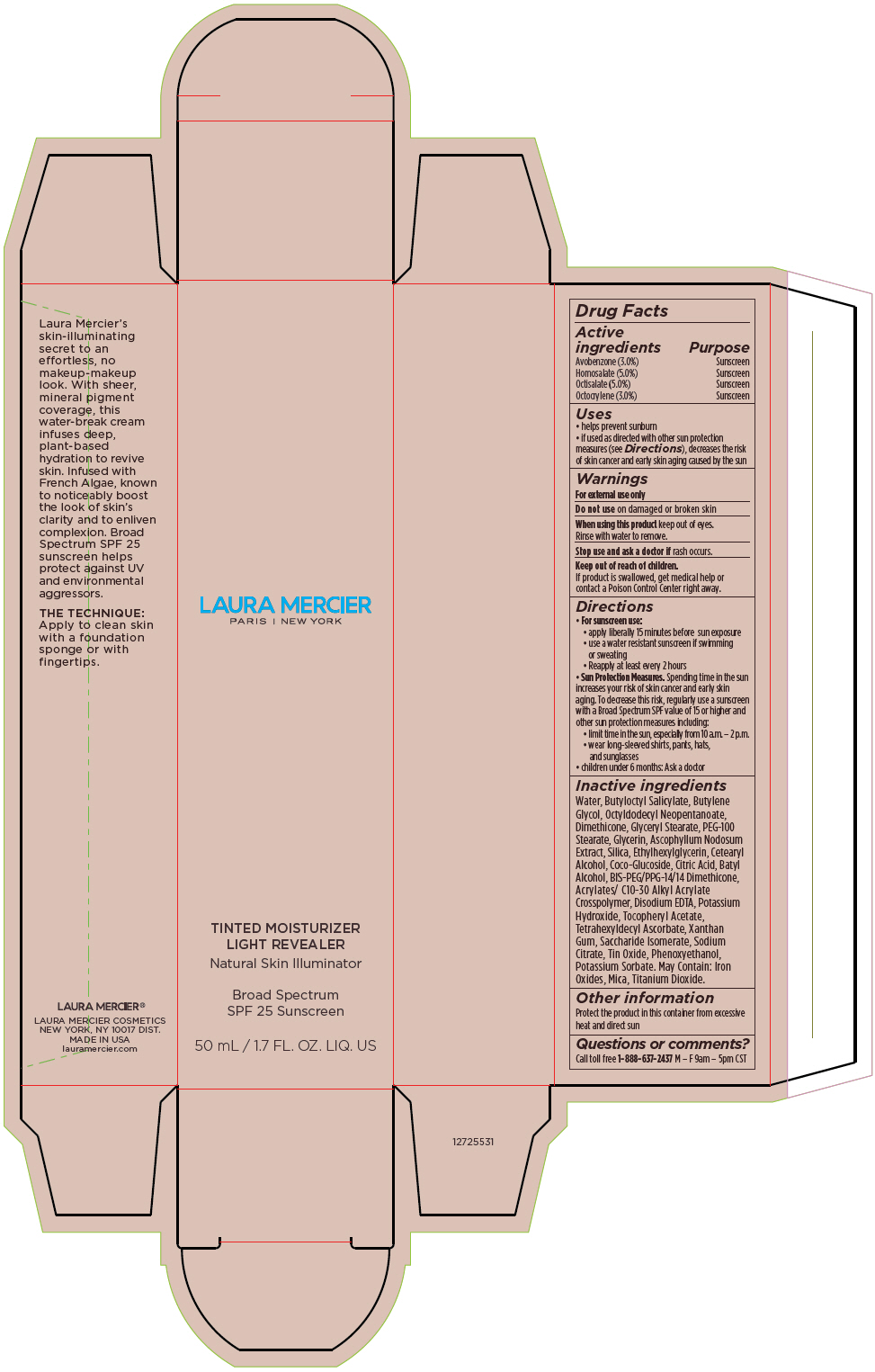 DRUG LABEL: Laura Mercier Tinted Moisturizer Light Revealer Natural Skin Illuminator Broad Spectrum SPF 25 Sunscreen 0N1 Petal
NDC: 82761-001 | Form: CREAM
Manufacturer: Laura Mercier US Buyer LLC
Category: otc | Type: HUMAN OTC DRUG LABEL
Date: 20231004

ACTIVE INGREDIENTS: AVOBENZONE 1.53 g/50 mL; HOMOSALATE 2.55 g/50 mL; OCTISALATE 2.55 g/50 mL; OCTOCRYLENE 1.53 g/50 mL
INACTIVE INGREDIENTS: WATER; BUTYLOCTYL SALICYLATE; BUTYLENE GLYCOL; OCTYLDODECYL NEOPENTANOATE; DIMETHICONE; GLYCERYL MONOSTEARATE; PEG-100 STEARATE; GLYCERIN; ASCOPHYLLUM NODOSUM; SILICON DIOXIDE; ETHYLHEXYLGLYCERIN; CETOSTEARYL ALCOHOL; COCO GLUCOSIDE; CITRIC ACID MONOHYDRATE; BATILOL; BIS-PEG/PPG-14/14 DIMETHICONE; CARBOMER INTERPOLYMER TYPE A (ALLYL SUCROSE CROSSLINKED); EDETATE DISODIUM; POTASSIUM HYDROXIDE; .ALPHA.-TOCOPHEROL ACETATE, DL-; TETRAHEXYLDECYL ASCORBATE; XANTHAN GUM; SACCHARIDE ISOMERATE; SODIUM CITRATE, UNSPECIFIED FORM; STANNIC OXIDE; PHENOXYETHANOL; POTASSIUM SORBATE; MICA; TITANIUM DIOXIDE; FERRIC OXIDE RED; FERRIC OXIDE YELLOW; FERROSOFERRIC OXIDE

Laura Mercier Tinted Moisturizer Light Revealer Natural Skin Illuminator Broad Spectrum SPF 25 Sunscreen

Drug Facts

ACTIVE INGREDIENT

Active ingredients | Purpose
Avobenzone (3.0%) | Sunscreen
Homosalate (5.0%) | Sunscreen
Octisalate (5.0%) | Sunscreen
Octocrylene (3.0%) | Sunscreen

Uses

- helps prevent sunburn
- if used as directed with other sun protection measures (see Directions), decreases the risk of skin cancer and early skin aging caused by the sun

Warnings

For external use only

Do not use on damaged or broken skin

When using this product keep out of eyes. Rinse with water to remove.

Stop use and ask a doctor if rash occurs.

Keep out of reach of children.

If product is swallowed, get medical help or contact a Poison Control Center right away.

Directions

- For sunscreen use:
  - apply liberally 15 minutes before sun exposure
  - use a water resistant sunscreen if swimming or sweating
  - Reapply at least every 2 hours
- Sun Protection Measures. Spending time in the sun increases your risk of skin cancer and early skin aging. To decrease this risk, regularly use a sunscreen with a Broad Spectrum SPF value of 15 or higher and other sun protection measures including:
  - limit time in the sun, especially from 10 a.m. – 2 p.m.
  - wear long-sleeved shirts, pants, hats, and sunglasses
- children under 6 months: Ask a doctor

Inactive ingredients

Water, Butyloctyl Salicylate, Butylene Glycol, Octyldodecyl Neopentanoate, Dimethicone, Glyceryl Stearate, PEG-100 Stearate, Glycerin, Ascophyllum Nodosum Extract, Silica, Ethylhexylglycerin, Cetearyl Alcohol, Coco-Glucoside, Citric Acid, Batyl Alcohol, BIS-PEG/PPG-14/14 Dimethicone, Acrylates/ C10-30 Alkyl Acrylate Crosspolymer, Disodium EDTA, Potassium Hydroxide, Tocopheryl Acetate, Tetrahexyldecyl Ascorbate, Xanthan Gum, Saccharide Isomerate, Sodium Citrate, Tin Oxide, Phenoxyethanol, Potassium Sorbate. May Contain: Iron Oxides, Mica, Titanium Dioxide.

Other information

Protect the product in this container from excessive heat and direct sun

Questions or comments?

Call toll free 1-888-637-2437 M – F 9am – 5pm CST

PRINCIPAL DISPLAY PANEL - 50 mL Tube Carton - 0N1 Petal

LAURA MERCIER
PARIS | NEW YORK

TINTED MOISTURIZER
LIGHT REVEALER

Natural Skin Illuminator

Broad Spectrum
SPF 25 Sunscreen

50 mL / 1.7 FL. OZ. LIQ. US

PRINCIPAL DISPLAY PANEL - 50 mL Tube Carton - 0W1 Pearl

LAURA MERCIER
PARIS | NEW YORK

TINTED MOISTURIZER
LIGHT REVEALER

Natural Skin Illuminator

Broad Spectrum
SPF 25 Sunscreen

50 mL / 1.7 FL. OZ. LIQ. US

PRINCIPAL DISPLAY PANEL - 50 mL Tube Carton - 1C0 Cameo

LAURA MERCIER
PARIS | NEW YORK

TINTED MOISTURIZER
LIGHT REVEALER

Natural Skin Illuminator

Broad Spectrum
SPF 25 Sunscreen

50 mL / 1.7 FL. OZ. LIQ. US

PRINCIPAL DISPLAY PANEL - 50 mL Tube Carton - 1W1 Porcelain

LAURA MERCIER
PARIS | NEW YORK

TINTED MOISTURIZER
LIGHT REVEALER

Natural Skin Illuminator

Broad Spectrum
SPF 25 Sunscreen

50 mL / 1.7 FL. OZ. LIQ. US

PRINCIPAL DISPLAY PANEL - 50 mL Tube Carton - 2N1 Nude

LAURA MERCIER
PARIS | NEW YORK

TINTED MOISTURIZER
LIGHT REVEALER

Natural Skin Illuminator

Broad Spectrum
SPF 25 Sunscreen

50 mL / 1.7 FL. OZ. LIQ. US

PRINCIPAL DISPLAY PANEL - 50 mL Tube Carton - 2W1 Natural

LAURA MERCIER
PARIS | NEW YORK

TINTED MOISTURIZER
LIGHT REVEALER

Natural Skin Illuminator

Broad Spectrum
SPF 25 Sunscreen

50 mL / 1.7 FL. OZ. LIQ. US

PRINCIPAL DISPLAY PANEL - 50 mL Tube Carton - 3N1 Sand

LAURA MERCIER
PARIS | NEW YORK

TINTED MOISTURIZER
LIGHT REVEALER

Natural Skin Illuminator

Broad Spectrum
SPF 25 Sunscreen

50 mL / 1.7 FL. OZ. LIQ. US

PRINCIPAL DISPLAY PANEL - 50 mL Tube Carton - 3W1 Bisque

LAURA MERCIER
PARIS | NEW YORK

TINTED MOISTURIZER
LIGHT REVEALER

Natural Skin Illuminator

Broad Spectrum
SPF 25 Sunscreen

50 mL / 1.7 FL. OZ. LIQ. US

PRINCIPAL DISPLAY PANEL - 50 mL Tube Carton - 4C1 Almond

LAURA MERCIER
PARIS | NEW YORK

TINTED MOISTURIZER
LIGHT REVEALER

Natural Skin Illuminator

Broad Spectrum
SPF 25 Sunscreen

50 mL / 1.7 FL. OZ. LIQ. US

PRINCIPAL DISPLAY PANEL - 50 mL Tube Carton - 4W1 Tawny

LAURA MERCIER
PARIS | NEW YORK

TINTED MOISTURIZER
LIGHT REVEALER

Natural Skin Illuminator

Broad Spectrum
SPF 25 Sunscreen

50 mL / 1.7 FL. OZ. LIQ. US

PRINCIPAL DISPLAY PANEL - 50 mL Tube Carton - 5N1 Walnut

LAURA MERCIER
PARIS | NEW YORK

TINTED MOISTURIZER
LIGHT REVEALER

Natural Skin Illuminator

Broad Spectrum
SPF 25 Sunscreen

50 mL / 1.7 FL. OZ. LIQ. US

PRINCIPAL DISPLAY PANEL - 50 mL Tube Carton - 5W1 Tan

LAURA MERCIER
PARIS | NEW YORK

TINTED MOISTURIZER
LIGHT REVEALER

Natural Skin Illuminator

Broad Spectrum
SPF 25 Sunscreen

50 mL / 1.7 FL. OZ. LIQ. US

PRINCIPAL DISPLAY PANEL - 50 mL Tube Carton - 6N1 Mocha

LAURA MERCIER
PARIS | NEW YORK

TINTED MOISTURIZER
LIGHT REVEALER

Natural Skin Illuminator

Broad Spectrum
SPF 25 Sunscreen

50 mL / 1.7 FL. OZ. LIQ. US

PRINCIPAL DISPLAY PANEL - 50 mL Tube Carton - 6C1 Cacao

LAURA MERCIER
PARIS | NEW YORK

TINTED MOISTURIZER
LIGHT REVEALER

Natural Skin Illuminator

Broad Spectrum
SPF 25 Sunscreen

50 mL / 1.7 FL. OZ. LIQ. US